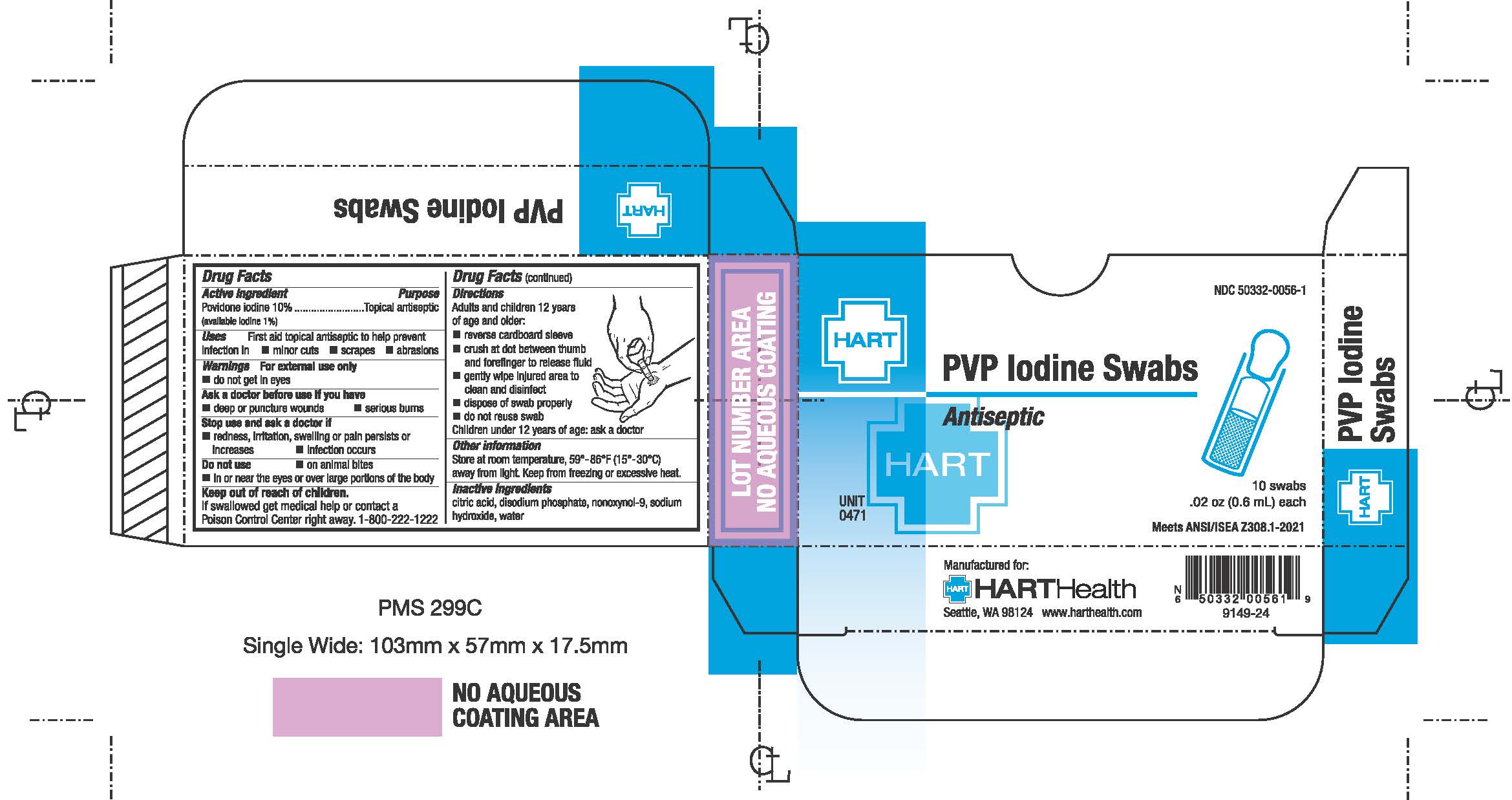 DRUG LABEL: POVIDONE-IODINE
NDC: 50332-0056 | Form: SOLUTION
Manufacturer: HART Health
Category: otc | Type: HUMAN OTC DRUG LABEL
Date: 20240215

ACTIVE INGREDIENTS: POVIDONE-IODINE 10 mg/1 mL
INACTIVE INGREDIENTS: CITRIC ACID MONOHYDRATE; SODIUM PHOSPHATE, DIBASIC, ANHYDROUS; NONOXYNOL-9; SODIUM HYDROXIDE; WATER

POVIDONE IODINE TOPICAL SOLUTION USP

Active Ingredient

Povidone Iodine 10% (available iodine 1%)

Purpose

Topical antiseptic

Uses

First aid topical antiseptic to help prevent infection in

- minor cuts
- scrapes
- abrasions

Warnings

For external use only.

- do not get in eyes

Ask a dcotor before use if you have

- deep or puncture wounds
- serious burns

Stop use and ask a doctor if

- redness, irritation, swelling or pain persists or increases
- infection occurs

Do not use

- on animal bits
- in or near the eyes or over large portions of the body

Keep out of reach of children.

If swallowed, get medical help immediately or contact a Poison Control Center right away. 1-800-222-1222

Directions

Adults and children 12 years of age and older:

- reverse cardboard sleeve
- crush at dot between thumb and forefinger to release fluid
- gently wipes injured area to clean and disinfect
- dispose of swab peoperly
- do not reuse swab

Children under 12 years of age: ask a doctor

Other information

Store at room temperaturem 59° - 86°F (15° - 30°C) away from light. Keep from freezing or excessive heat.

Inactive ingredients

citric acid, disodium phosphate, nonoxynol-9, sodium hydroxide, water.